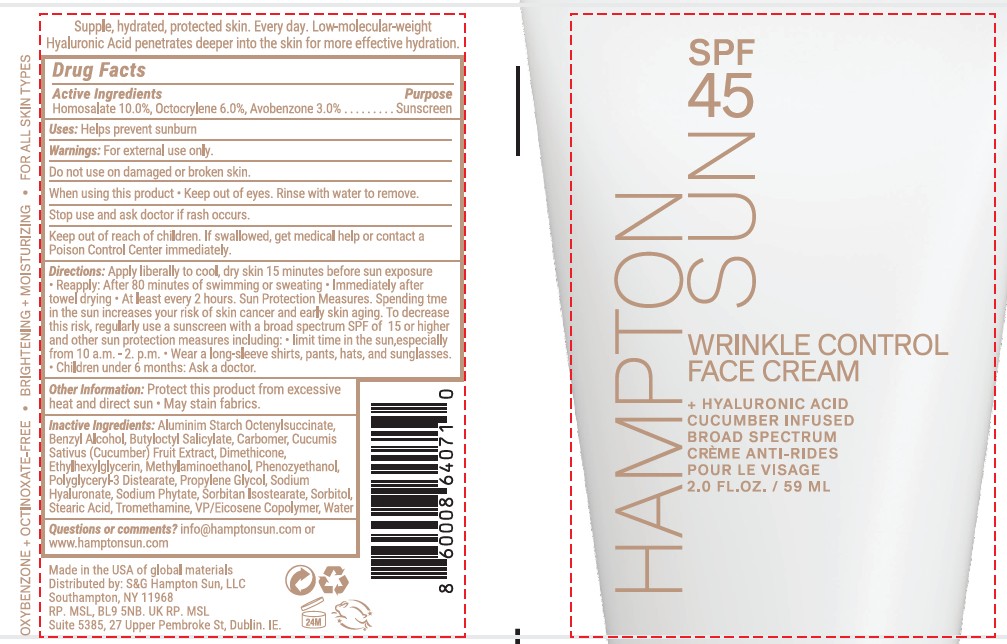 DRUG LABEL: Homosalate 10 Avobenzone 3%  Octocrylene 6%
NDC: 87170-003 | Form: LOTION
Manufacturer: S&C Hampton Sun LLC
Category: otc | Type: HUMAN OTC DRUG LABEL
Date: 20260126

ACTIVE INGREDIENTS: OCTOCRYLENE 6 g/100 mL; HOMOSALATE 10 g/100 mL; AVOBENZONE 3 g/100 mL
INACTIVE INGREDIENTS: ALUMINUM STARCH OCTENYLSUCCINATE; AMINOMETHYLPROPANOL; ARACHIDIC ACID; BENZYL ALCOHOL; BUTYLOCTYL SALICYLATE; CARBOMER; CELLULOSE GUM; DIMETHICONE; ETHYLHEXYLGLYCERIN; GLYCERIN; LAURIC ACID; MYRISTIC ACID; PALMITIC ACID; PHENOXYETHANOL; SODIUM HYALURONATE; SODIUM PHYTATE; SODIUM POLYACRYLATE (8000 MW); SORBITAN ISOSTEARATE; SORBITOL; STEARIC ACID; VINYLPYRROLIDONE/EICOSENE COPOLYMER; WATER; BROWN IRON OXIDE

Hampton Sun SPF 45 Face Creamwith cucumber frangrance

Active Ingredients

Homosalate 10%;Avobenzone 3%; Octocrylene 6%

Purpous

Sunscreen

Uses

Helps prevent sunburn

Directions

• apply liberally and spread evenly by hand 15 minutes before sun exposure • reapply: • after 80 minutes of swimming or sweating • immediately after towel drying • at least every 2 hours

• Sun Protection Measures. Spending tme in the sun increases your risk of skin cancer and early skin aging. To decrease this risk, regularly use a sunscreen with a broad spectrum SPF of 15 or higher and other sun protection measures including: • limit time in the sun, especially from
10 a.m. - 2. p.m. • wear a long-sleeve shirt, pants, hats, and sunglasses.
• children under 6 months: Ask a doctor.

Warning

For external use only.

Do not useon damaged or broken skin.
When using this product• keep out of eyes. Rinse with water to remove.

Stop use and ask doctor ifrash occurs.

Inactive Ingredients

ALUMINUM STARCH OCTENYLSUCCINATE
AMINOMETHYLPROPANOL
ARACHIDIC ACID
BENZYL ALCOHOL
BUTYLOCTYL SALICYLATE
CARBOMER
CELLULOSE GUM
DIMETHICONE
ETHYLHEXYLGLYCERIN
GLYCERIN
LAURIC ACID
MYRISTIC ACID
PALMITIC ACID
PHENOXYETHANOL
SODIUM HYALURONATE
SODIUM PHYTATE
SODIUM POLYACRYLATE
SORBITAN ISOSTEARATE
SORBITOL
STEARIC ACID
VP/EICOSENE COPOLYMER
WATER
OXIDES